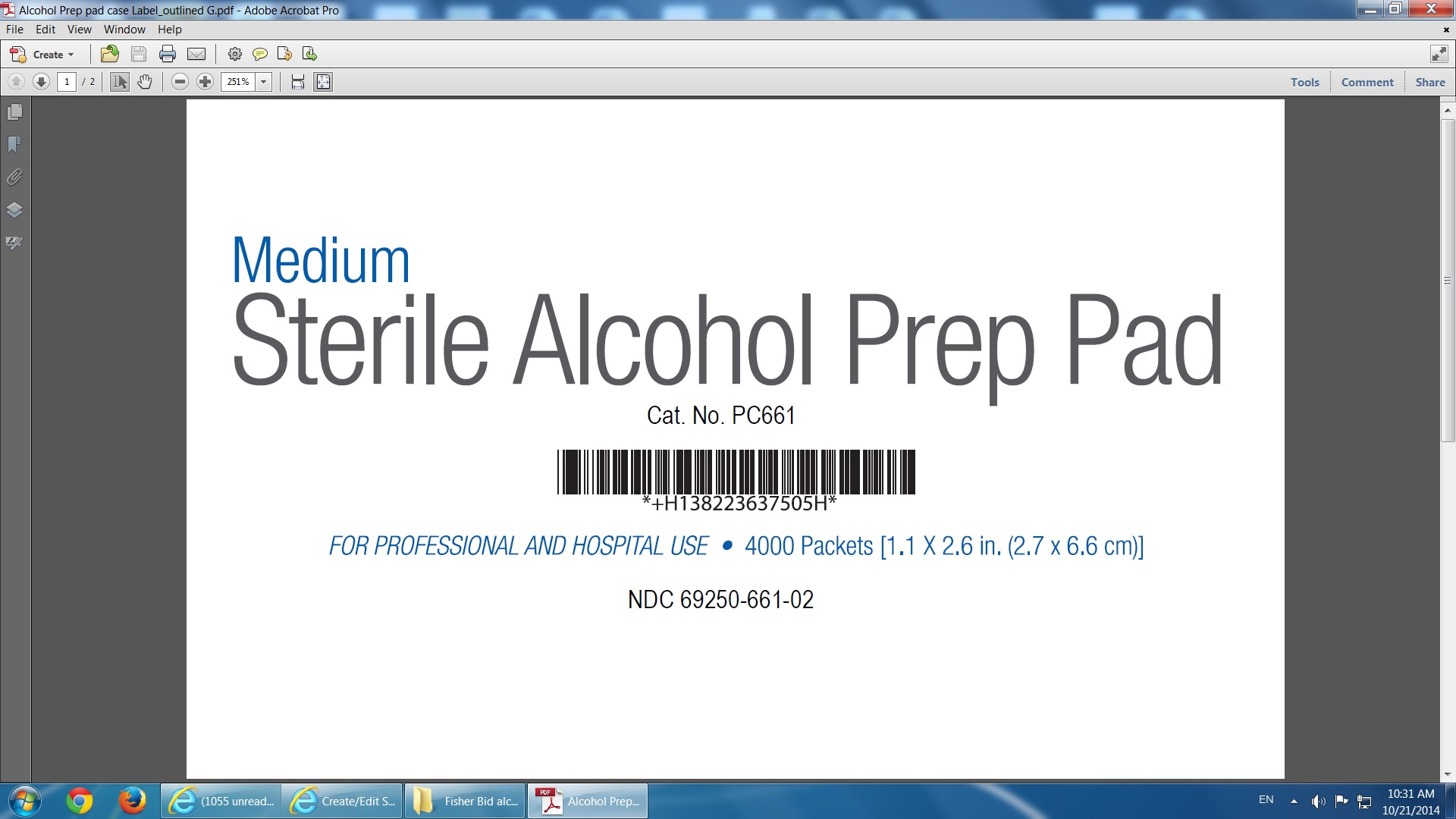 DRUG LABEL: Alcohol Prep Pad
NDC: 69250-661 | Form: SPONGE
Manufacturer: BioMed Resource Inc.
Category: otc | Type: HUMAN OTC DRUG LABEL
Date: 20240110

ACTIVE INGREDIENTS: Isopropyl Alcohol 7 mL/10 mL
INACTIVE INGREDIENTS: water

Alcohol Prep pad

Alcohol Prep Pad

70% Isoprppyl Alcohol

PURPOSE

Antispectic. For preparation of skin prior of injection.

KEEP OUT OF REACH OF CHILDREN

In case of accidental ingestion, contact your phisician or Poison Control Center right away.

Do not use with electrocautery procedures.

INACTIVE INGREDIENT

Purified water.

DOSAGE AND ADMINISTRATION

One piece at the time, Discard after use.

INDICATIONS AND USAGE

Wipe injection site vigorously.Discard after use.

WARNINGS

1. For external use only;

2. Flammable. Keep away from heat or flame;

3. Aviod to contact eyes. Flush throoughly with water in case of contact;

4. Stop use if irritation or redness develop;

5. Do not use with electrocautery procedures;

Keep out of reach of children.